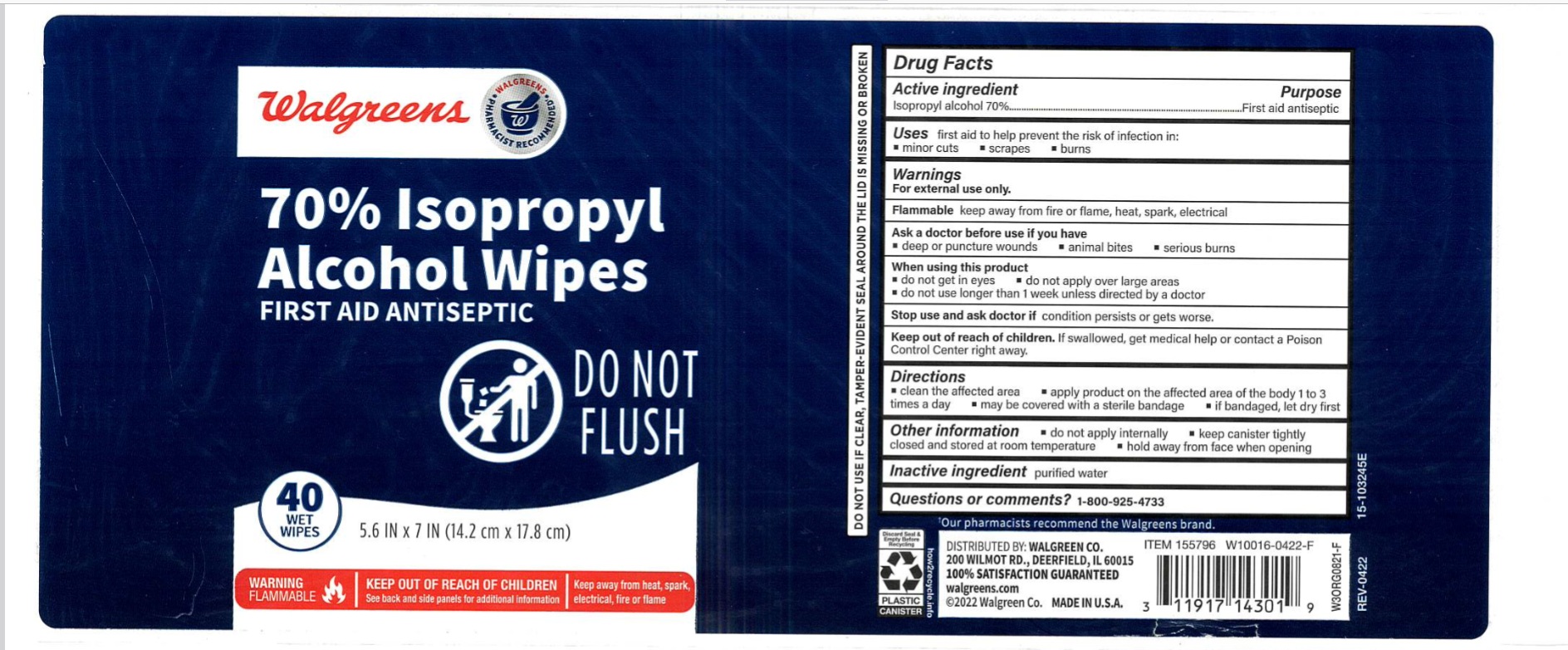 DRUG LABEL: Walgreens 70% Isopropyl Alcohol Wipes
NDC: 0363-6505 | Form: CLOTH
Manufacturer: Walgreen Company
Category: otc | Type: HUMAN OTC DRUG LABEL
Date: 20260219

ACTIVE INGREDIENTS: ISOPROPYL ALCOHOL 70 mL/100 mL
INACTIVE INGREDIENTS: WATER

Walgreens 70% Isopropyl Alcohol Wipes

Active ingredient

Isopropyl alcohol 70%

Purpose

First aid antiseptic

Uses

first aid to help prevent the risk of infection in:

- minor cuts
- scrapes
- burns

Warnings

For external use only.

Flammable keep away from fire or flame, heat, spark, electrical

Ask a doctor before use if you have

- deep or puncture wounds
- animal bites
- serious burns

When using this product

- do not get in eyes
- do not apply over large areas
- do not use longer than 1 week unless directed by a doctor

Stop use and ask doctor if

condition persists or gets worse.

Keep out of reach of children.

If swallowed, get medical help or contact a Poison Control Center right away.

Directions

- clean the affected area
- apply product on the affected area of the body 1 to 3 times a day
- may be covered with a sterile bandage
- if bandaged, let dry first

Other information

- do not apply internally
- keep canister tightly closed and stored at room temperature
- hold away from face when opening

Inactive ingredient

purified water

Questions or comments?

1-800-925-4733